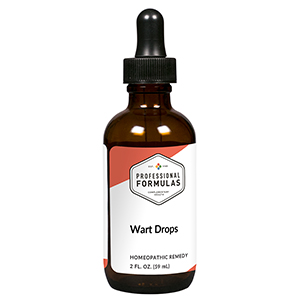 DRUG LABEL: Wart Drops
NDC: 63083-2078 | Form: LIQUID
Manufacturer: Professional Complementary Health Formulas
Category: homeopathic | Type: HUMAN OTC DRUG LABEL
Date: 20190815

ACTIVE INGREDIENTS: LACTIC ACID, DL- 4 [hp_X]/59 mL; SCROPHULARIA NODOSA WHOLE 4 [hp_X]/59 mL; CAUSTICUM 6 [hp_X]/59 mL; THUJA OCCIDENTALIS LEAF 6 [hp_X]/59 mL; OYSTER SHELL CALCIUM CARBONATE, CRUDE 12 [hp_X]/59 mL; SOLANUM DULCAMARA WHOLE 12 [hp_X]/59 mL; NAJA NAJA VENOM 12 [hp_X]/59 mL; SODIUM SULFATE 12 [hp_X]/59 mL
INACTIVE INGREDIENTS: ALCOHOL; WATER

C78

ACTIVE INGREDIENTS

Lacticum acidum 4X
Scrophularia nodosa 4X
Causticum 6X, 12X
Thuja occidentalis 6X, 12X
Calcarea carbonica 12X
Dulcamara 12X
Naja tripudians 12X
Natrum sulphuricum 12X

QUESTIONS

Professional Formulas

PO Box 2034 Lake Oswego, OR 97035

INDICATIONS

For the temporary relief of small growths on, or thickening of the skin.*

PURPOSE

*Claims based on traditional homeopathic practice, not accepted medical evidence. Not FDA evaluated.

WARNINGS

Consult a doctor if condition worsens or if symptoms persist. Keep out of the reach of children. In case of overdose, get medical help or contact a poison control center right away. If pregnant or breastfeeding, ask a healthcare professional before use.

Keep out of the reach of children.

PREGNANCY OR BREAST FEEDING

If pregnant or breastfeeding, ask a healthcare professional before use.

DIRECTIONS

Place drops under tongue 30 minutes before/after meals. Adults and children 12 years and over: Take 10 drops up to 3 times per day. Consult a physician for use in children under 12 years of age.

OTHER INFORMATION

Tamper resistant. If seal is broken, do not use. After opening, close container tightly and store at room temperature away from heat.

INACTIVE INGREDIENTS

20% ethanol, purified water.

LABEL

Est 1985

Professional Formulas

Complementary Health

Wart Drops

Homeopathic Remedy

2 FL. OZ. (59 mL)